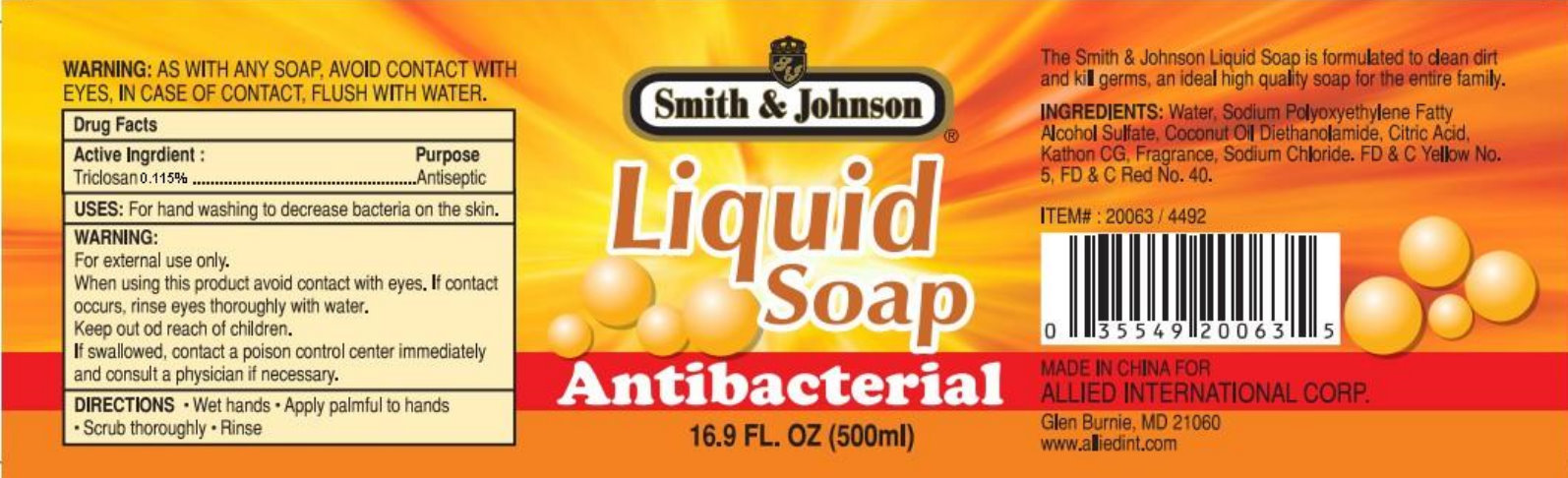 DRUG LABEL: Smith and Johnson Antibacterial
NDC: 52546-110 | Form: SOAP
Manufacturer: Allied International Corp
Category: otc | Type: HUMAN OTC DRUG LABEL
Date: 20110519

ACTIVE INGREDIENTS: TRICLOSAN 0.115 mL/100 mL
INACTIVE INGREDIENTS: WATER; SODIUM LAURETH-2 SULFATE; COCONUT OIL; DIETHANOLAMINE; CITRIC ACID MONOHYDRATE; SODIUM CHLORIDE; FD&C YELLOW NO. 5; FD&C RED NO. 40

Smith & Johnson Liquid Soap Antibacterial

Drug Facts

Active Ingredient

Triclosan 0.115%

Purpose

Antiseptic

INDICATIONS AND USAGE

USES: For hand washing to decrease bacteria on the skin.

WARNING:

For external use only.

When using this product avoid contact with eyes. If contact occurs, rinse eyes thoroughly with water.

Keep out of reach of children.

ASK DOCTOR

If swallowed, contact a poison control center immediately and consult a physician if necessary.

DIRECTIONS

- Wet hands
- Apply palmful to hands
- Scrub thoroughly
- Rinse

WARNINGS AND PRECAUTIONS

WARNING: AS WITH ANY SOAP, AVOID CONTACT WITH EYES, IN CASE OF CONTACT, FLUSH WITH WATER.

DESCRIPTION

The Smith and Johnson Liquid Soap is formulated to clean dirt and kill germs, an ideal high quality soap for the entire family.

INACTIVE INGREDIENT

INGREDIENTS: Water, Sodium Polyoxyethylene Fatty Alcohol Sulfate, Coconut Oil Diethanolamide, Citric Acid, Kathon CG, Fragrance, Sodium Chloride, FD and C Yellow No.5, FD and C Red No.40.

ITEM Number: 20063 / 4492

MADE IN CHINA FOR

ALLIED INTERNATIONAL CORP.

Glen Burnie, MD 21060

www.alliedint.com

PACKAGE LABEL

Smith and Johnson

Liquid Soap

Antibacterial

16.9 FL.OZ (500ml)